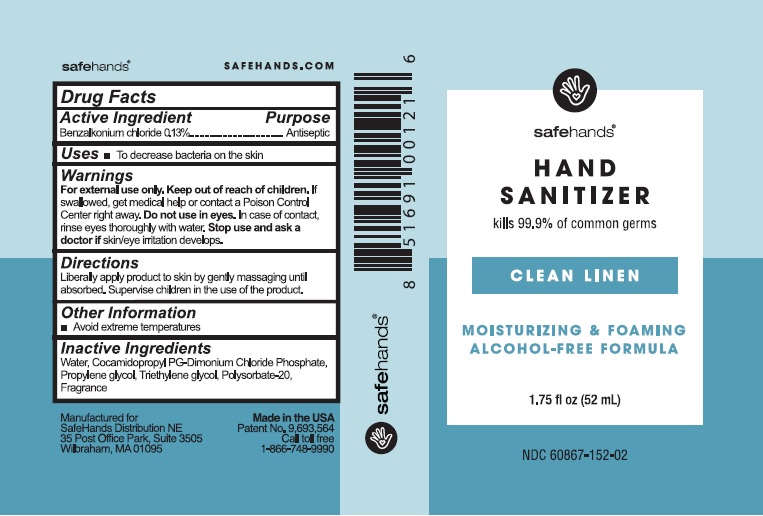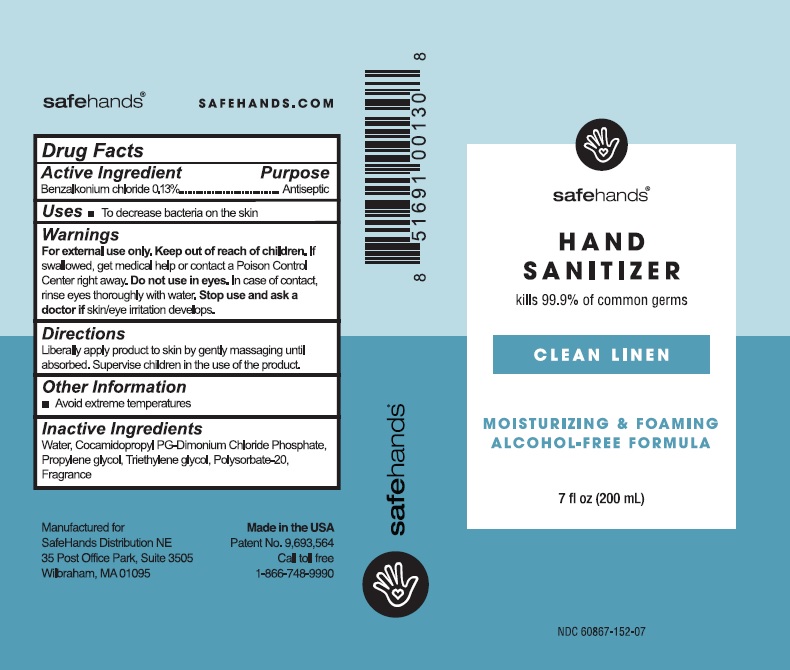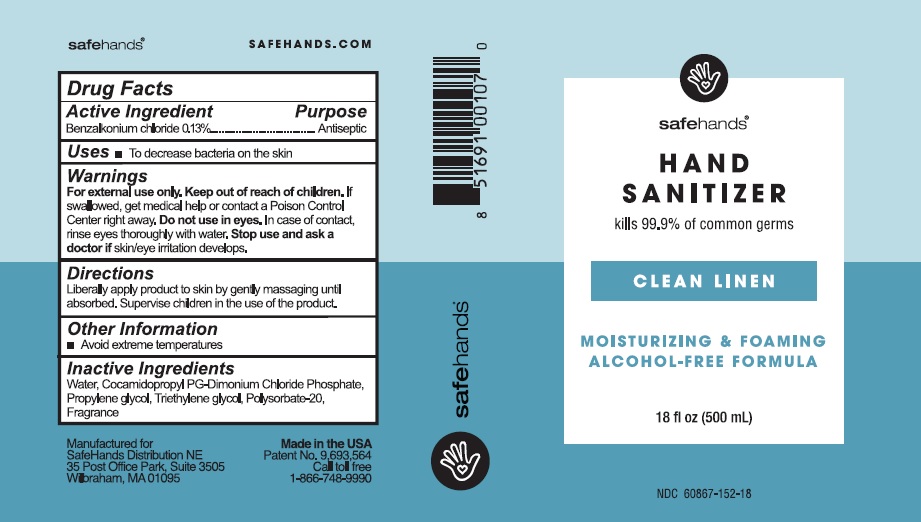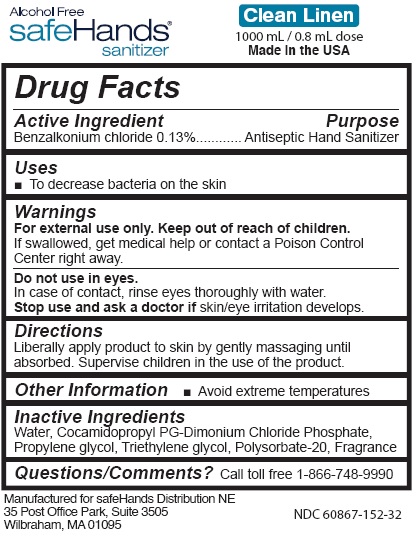 DRUG LABEL: safeHands Hand Sanitizer Clean Linen
NDC: 60867-152 | Form: LIQUID
Manufacturer: Safehands Distribution Ne, LLC
Category: otc | Type: HUMAN OTC DRUG LABEL
Date: 20251129

ACTIVE INGREDIENTS: BENZALKONIUM CHLORIDE 0.13 g/100 mL
INACTIVE INGREDIENTS: Water; COCAMIDOPROPYL PG-DIMONIUM CHLORIDE PHOSPHATE; PROPYLENE GLYCOL; TRIETHYLENE GLYCOL; POLYSORBATE 20

safeHands Hand Sanitizer Clean Linen

Active Ingredient

Benzalkonium chloride 0.13%

Purpose

Antiseptic

Uses

To decrease bacteria on the skin

Warnings

For external use only.

Keep out of reach of children.

If swallowed, get medical help or contact a Poison Control Center right away.

Do not use in eyes.

In case of contact, rinse eyes thoroughly with water.

Stop use and ask a doctor

if skin/eye irritation develops.

Directions

Liberally apply product to skin by gently massaging until

absorbed. Supervise children in the use of this product.

Other Information

• Avoid extreme temperatures.

Inactive Ingredients

Water, Cocamidolpropyl PG-Dimonium Chloride Phospate,

Propylene glycol, Triethylene glycol, Polysorbate-20, Fragrance

Package Labeling

safeHands®
Hand Sanitizer

kills 99.9% of common germs

CLEAN LINEN

MOISTURIZING & FOAMING

ALCOHOL-FREE FORMULA

1.75 fl oz (52 mL)

NDC 60867-152-02

Manufactured for

safeHands Distribution NE

35 Post Oak Office Park, Suite 3505

Wilbraham, MA 01095

Call toll free

1-866-748-9990

SAFEHANDS.COM

1.75 fl oz

7 fl oz

18 fl oz

1000 mL

res